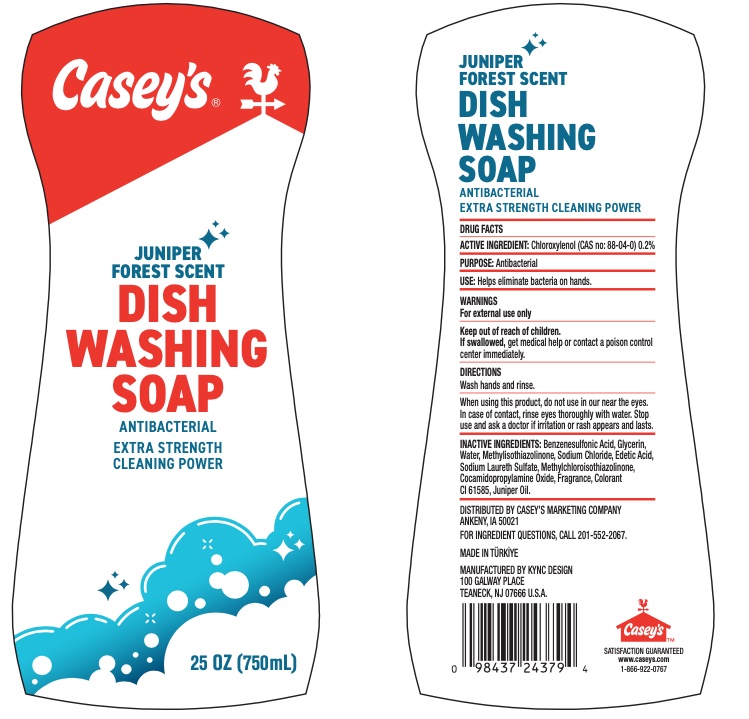 DRUG LABEL: CaseysDishwashingSoap
NDC: 76557-050 | Form: LIQUID
Manufacturer: KYNC DESIGN LLC
Category: otc | Type: HUMAN OTC DRUG LABEL
Date: 20260123

ACTIVE INGREDIENTS: CHLOROXYLENOL 0.2 g/100 g
INACTIVE INGREDIENTS: P-DODECYLBENZENESULFONIC ACID; GLYCERIN; WATER; COCAMIDOPROPYLAMINE OXIDE; SODIUM CHLORIDE; EDETIC ACID; SODIUM LAURETH SULFATE; METHYLCHLOROISOTHIAZOLINONE; METHYLISOTHIAZOLINONE; JUNIPER BERRY OIL

Caseys Dishwashing Soap

Active Ingredient

Chloroxylenol (CAS no: 88-04-0) 0.2%

Use

helps eliminate bacteria on hands

Warnings

For external use only

Keep out of reach of children.

If swallowed, get medical help or contact a Poison Control Center right away.

Directions

wash hands and rinse

When using this product

do not use in or near the eyes. In case of contact, rinse eyes thoroughly with water.

Stop use and ask a doctor if irritation or rash appears and lasts.

Inactive Ingredients

Benzenesulfonic Acid, Glycerin, Water, Methylisothiazolinone, Sodium Chloride, Edetic Acid, Sodium Laureth Sulfate, Methylchloroisothiazolinone, Cocamidopropylamine Oxide, Fragrence, Colorant CI 61585, Juniper Oil.

PURPOSE

Antibacterial